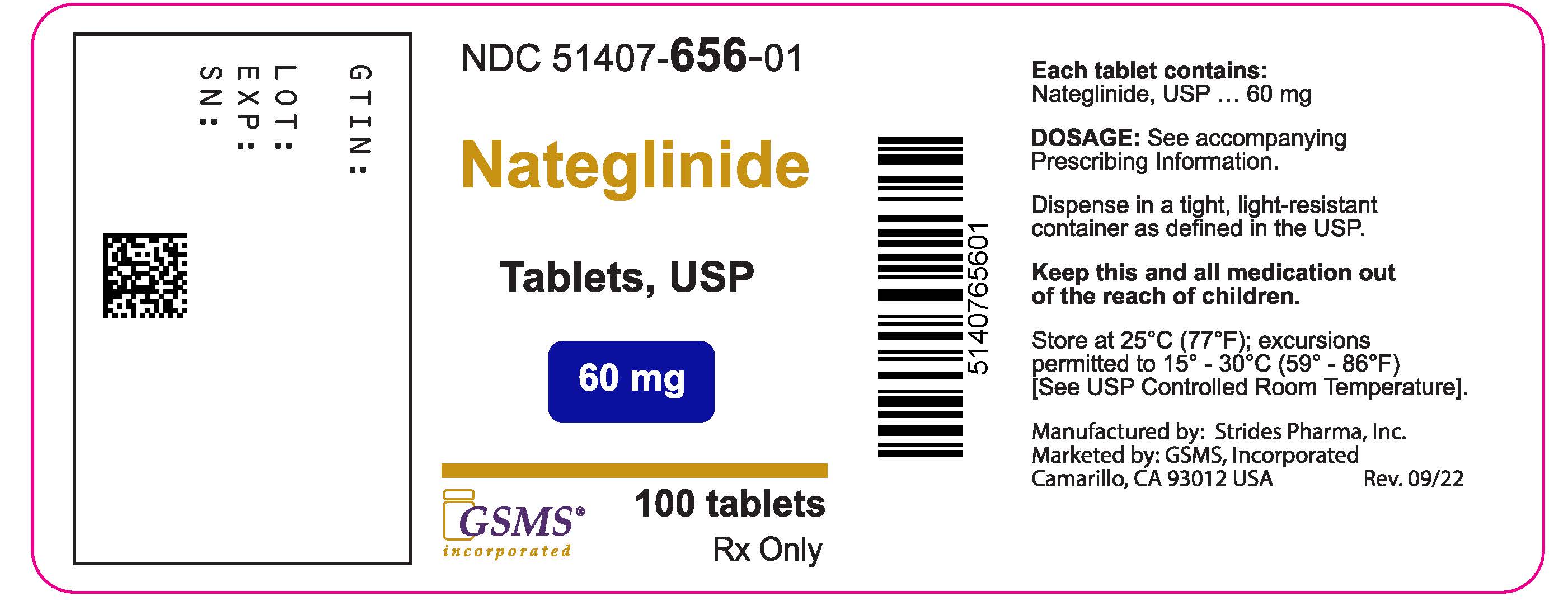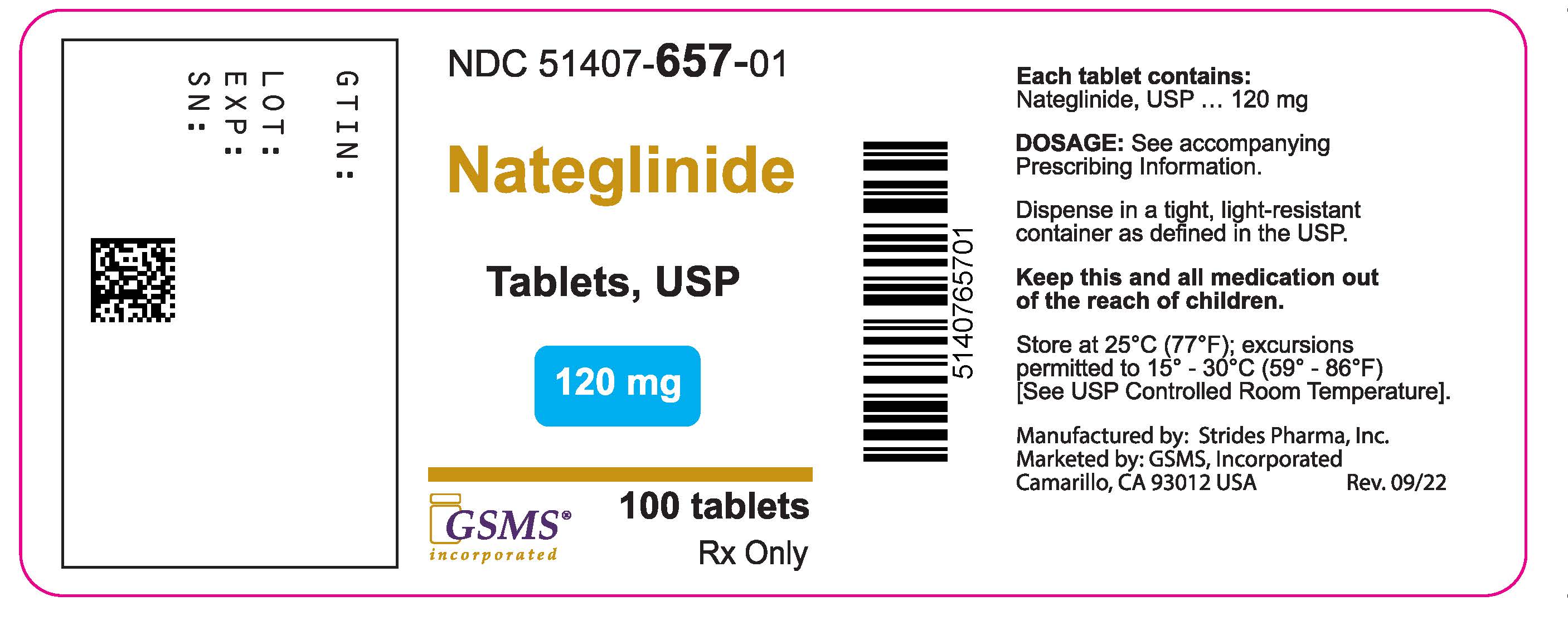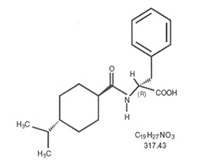 DRUG LABEL: Nateglinide
NDC: 51407-657 | Form: TABLET
Manufacturer: Golden State Medical Supply, Inc.
Category: prescription | Type: HUMAN PRESCRIPTION DRUG LABEL
Date: 20250415

ACTIVE INGREDIENTS: NATEGLINIDE 120 mg/1 1
INACTIVE INGREDIENTS: SILICON DIOXIDE; CROSCARMELLOSE SODIUM; LACTOSE MONOHYDRATE; MAGNESIUM STEARATE; POVIDONE; FD&C YELLOW NO. 6; CELLULOSE, MICROCRYSTALLINE; FERRIC OXIDE YELLOW

HIGHLIGHTS OF PRESCRIBING INFORMATION

NATEGLINIDE TABLETS. These highlights do not include all the information needed to use NATEGLINIDE TABLETS safely and effectively. See full prescribing information for NATEGLINIDE TABLETS.
NATEGLINIDE tablets, for oral use
Initial U.S. Approval: 2000

1 INDICATIONS AND USAGE

Nateglinide is a glinide indicated as an adjunct to diet and exercise to improve glycemic control in adults with type 2 diabetes mellitus. (1)

Limitations of Use: Not for treating type 1 diabetes mellitus or diabetes ketoacidosis (1)

2 DOSAGE AND ADMINISTRATION

- Recommended dose is 120 mg three times daily (2)
- In patients who are near glycemic goal when treatment is initiated, 60 mg three times daily may be administered. (2)
- Administer 1 to 30 minutes before meals (2)
- If a meal is skipped, skip the scheduled dose to reduce the risk of hypoglycemia. (2, 5.1)

3 DOSAGE FORMS AND STRENGTHS

Tablets: 60 mg and 120 mg (3)

4 CONTRAINDICATIONS

- History of hypersensitivity to nateglinide or its inactive ingredients (4)

5 WARNINGS AND PRECAUTIONS

- Hypoglycemia:Nateglinide may cause hypoglycemia. Administer before meals to reduce the risk of hypoglycemia. Skip the scheduled dose of nateglinide if a meal is skipped to reduce the risk of hypoglycemia. (5.1)
- Macrovascular Outcomes:There have been no clinical studies establishing conclusive evidence of macrovascular risk reduction with nateglinide. (5.2)

6 ADVERSE REACTIONS

- Common adverse reactions associated with nateglinide (3% or greater incidence) were upper respiratory tract infection, back pain, flu symptoms, dizziness, arthropathy, diarrhea. (6.1)

To report SUSPECTED ADVERSE REACTIONS, contact Strides Pharma Inc at 1-877-244-9825 or FDA at 1-800-FDA-1088 or www.fda.gov/medwatch.

7 DRUG INTERACTIONS

- Drugs That May Increase the Potential for Hypoglycemia:Nateglinide dose reductions and increased frequency of glucose monitoring may be required when co-administered (7)
- Drugs That May Increase the Potential for Hyperglycemia:Nateglinide dose increases and increased frequency of glucose monitoring may be required when co-administered (7)
- Drugs That May Blunt Signs and Symptoms of Hypoglycemia:Increased frequency of glucose monitoring may be required when co-administered (7)

8 USE IN SPECIFIC POPULATIONS

- Lactation:Nateglinide is not recommended when breastfeeding (8.2)

FULL PRESCRIBING INFORMATION

1 INDICATIONS AND USAGE

Nateglinide is indicated as an adjunct to diet and exercise to improve glycemic control in adults with type 2 diabetes mellitus.

Limitations of Use:

Nateglinide should not be used in patients with type 1 diabetes mellitus or for the treatment of diabetic ketoacidosis.

2 DOSAGE AND ADMINISTRATION

The recommended dose of nateglinide is 120 mg orally three times daily before meals.

The recommended dose of nateglinide is 60 mg orally three times daily before meals in patients who are near glycemic goal when treatment is initiated.

Instruct patients to take nateglinide 1 to 30 minutes before meals.

In patients who skip meals, instruct patients to skip the scheduled dose of nateglinide to reduce the risk of hypoglycemia [see Warnings and Precautions (5.1)].

3 DOSAGE FORMS AND STRENGTHS

- 60 mg tablets: Pink color coated, round biconvex, beveled edge tablet debossed with "P 984" on one side and plain on the other side
- 120 mg tablets: Orange color coated, oval shaped biconvex, tablet debossed with "P 985" on one side and plain on the other side

4 CONTRAINDICATIONS

Nateglinide tablets are contraindicated in patients with a history of hypersensitivity to nateglinide or its inactive ingredients.

5 WARNINGS AND PRECAUTIONS

5.1 Hypoglycemia

All glinides, including nateglinide, can cause hypoglycemia [see Adverse Reactions (6.1)]. Severe hypoglycemia can cause seizures, may be life-threatening, or cause death. Hypoglycemia can impair concentration ability and reaction time; this may place an individual and others at risk in situations where these abilities are important (e.g., driving or operating other machinery).

Hypoglycemia can happen suddenly and symptoms may differ in each individual and change over time in the same individual. Symptomatic awareness of hypoglycemia may be less pronounced in patients with longstanding diabetes, in patients with diabetic neuropathy (nerve disease), in patients using medications that block the sympathetic nervous system (e.g., beta-blockers) [see Drug Interactions (7)], or in patients who experience recurrent hypoglycemia.

Factors which may increase the risk of hypoglycemia include changes in meal pattern (e.g., macronutrient content), changes in level of physical activity, changes to coadministered medication [see Drug Interactions (7)], and concomitant use with other antidiabetic agents. Patients with renal or hepatic impairment may be at higher risk of hypoglycemia [see Use in Specific Populations (8.6, 8.7), Clinical Pharmacology (12.3)].

Patients should take nateglinide before meals and be instructed to skip the dose of nateglinide if a meal is skipped [see Dosage and Administration (2)]. Patients and caregivers must be educated to recognize and manage hypoglycemia. Self-monitoring of blood glucose plays an essential role in the prevention and management of hypoglycemia. In patients at higher risk for hypoglycemia and patients who have reduced symptomatic awareness of hypoglycemia, increased frequency of blood glucose monitoring is recommended.

5.2 Macrovascular Outcomes

There have been no clinical studies establishing conclusive evidence of macrovascular risk reduction with nateglinide.

6 ADVERSE REACTIONS

The following serious adverse reaction is also described elsewhere in the labeling:

- Hypoglycemia [see Warnings and Precautions (5.1)]

6.1 Clinical Trials Experience

Because clinical trials are conducted under widely varying conditions, adverse reaction rates observed in the clinical trials of a drug cannot be directly compared to rates in the clinical trials of another drug and may not reflect the rates observed in practice.

In clinical trials, approximately 2,600 patients with type 2 diabetes mellitus were treated with nateglinide. Of these, approximately 1,335 patients were treated for 6 months or longer and approximately 190 patients for one year or longer. Table 1 shows the most common adverse reactions associated with nateglinide.

Table 1: Adverse Reactions other than Hypoglycemia (%) occurring Greater than or Equal to 2% in Nateglinide-Treated Patients from Pool of 12 to 64 week Placebo Controlled Trials
 | Placebo N = 458 | Nateglinide N = 1441
Preferred Term
Upper Respiratory Infection | 8.1 | 10.5
Back Pain | 3.7 | 4.0
Flu Symptoms | 2.6 | 3.6
Dizziness | 2.2 | 3.6
Arthropathy | 2.2 | 3.3
Diarrhea | 3.1 | 3.2
Accidental Trauma | 1.7 | 2.9
Bronchitis | 2.6 | 2.7
Coughing | 2.2 | 2.4

Hypoglycemia

Episodes of severe hypoglycemia (plasma glucose less than 36 mg/dL) were reported in two patients treated with nateglinide. Non-severe hypoglycemia occurred in 2.4 % of nateglinide treated patients and 0.4 % of placebo-treated patients [see Warnings and Precautions (5.1)].

Weight Gain

Patients treated with nateglinide had statistically significant mean increases in weight compared to placebo. In clinical trials, the mean weight increases with nateglinide 60 mg (3 times daily) and nateglinide 120 mg (3 times daily) compared to placebo were 1.0 kg and 1.6 kg, respectively.

Laboratory Test

Increases in Uric Acid:There were increases in mean uric acid levels for patients treated with nateglinide alone, nateglinide in combination with metformin, metformin alone, and glyburide alone. The respective differences from placebo were 0.29 mg/dL, 0.45 mg/dL, 0.28 mg/dL, and 0.19 mg/dL.

6.2 Postmarketing Experience

The following adverse reactions have been identified during post-approval use of nateglinide. Because these reactions are reported voluntarily from a population of uncertain size, it is not always possible to reliably estimate their frequency or establish a causal relationship to drug exposure.

- Hypersensitivity Reactions:Rash, itching, and urticaria
- Hepatobiliary Disorders:Jaundice, cholestatic hepatitis, and elevated liver enzymes

7 DRUG INTERACTIONS

Table 2 includes a list of drugs with clinically important drug interactions when concomitantly administered or withdrawn with nateglinide and instructions for managing or preventing them.

Table 2: Clinically Significant Drug Interactions with Nateglinide
Drugs That May Increase the Blood-Glucose-Lowering Effect of Nateglinide and Susceptibility to Hypoglycemia
Drugs: | Nonsteroidal anti-inflammatory drugs (NSAIDs), salicylates, monoamine oxidase inhibitors, non-selective beta-adrenergic-blocking agents, anabolic hormones (e.g., methandrostenolone), guanethidine, gymnema sylvestre, glucomannan, thioctic acid, and inhibitors of CYP2C9 (e.g., amiodarone, fluconazole, voriconazole, sulfinpyrazone) or in patients known to be poor metabolizers of CYP2C9 substrates, alcohol.
Intervention: | Dose reductions and increased frequency of glucose monitoring may be required when nateglinide is coadministered with these drugs.
Drugs and Herbals That May Reduce the Blood-Glucose-Lowering Effect of Nateglinide and Increase Susceptibility to Hyperglycemia
Drugs: | Thiazides, corticosteroids, thyroid products, sympathomimetics, somatropin, somatostatin analogues (e.g., lanreotide, octreotide), and CYP inducers (e.g., rifampin, phenytoin and St John's Wort).
Intervention: | Dose increases and increased frequency of glucose monitoring may be required when nateglinide is coadministered with these drugs.
Drugs That May Blunt Signs and Symptoms of Hypoglycemia
Drugs: | beta-blockers, clonidine, guanethidine, and reserpine
Intervention: | Increased frequency of glucose monitoring may be required when nateglinide is coadministered with these drugs.

8 USE IN SPECIFIC POPULATIONS

8.1 Pregnancy

Risk Summary

The available data from published literature and the applicant's pharmacovigilance with use of nateglinide in pregnant women are insufficient to identify a drug-associated risk of major birth defects, miscarriage or other adverse maternal or fetal outcomes. There are risks to the mother and fetus associated with poorly controlled diabetes in pregnancy (see Clinical Considerations). Nateglinide should be used during pregnancy only if the potential benefit justifies the potential risk to the fetus. In animal reproduction studies, there was no teratogenicity in rats and rabbits administered oral nateglinide during organogenesis at approximately 27 and 8 times the maximum recommended human dose (MRHD), respectively, based on body surface area (BSA).

The estimated background risk of major birth defects is 6% to 10% in women with pre-gestational diabetes with a HbA1c > 7 and has been reported to be as high as 20% to 25% in women with a HbA1c > 10. The estimated background risk of miscarriage for the indicated population is unknown. In the U.S. general population, the estimated background risk of major birth defects and miscarriage in clinically recognized pregnancies is 2% to 4% and 15% to 20%, respectively.

Clinical Considerations

Disease-Associated Maternal and/or Embryo/Fetal Risk

Poorly controlled diabetes in pregnancy increases the maternal risk for diabetic ketoacidosis, pre-eclampsia, spontaneous abortions, preterm delivery, and delivery complications. Poorly controlled diabetes increases the fetal risk for major birth defects, stillbirth, and macrosomia related morbidity.

Data

Animal data

In embryofetal development studies, nateglinide administered orally during the period of organogenesis was not teratogenic in rats at doses up to 1,000 mg/kg (corresponding to 27 times the MRHD of 120 mg three times per day, based on BSA). In rabbits, embryonic development was adversely affected at 500 mg/kg/day and the incidence of gallbladder agenesis or small gallbladder was increased at a dose of 300 and 500 mg/kg (corresponding to 16 and 27 times the MRHD). No such effects were observed at 150 mg/kg/day (corresponding to 8 times the MRHD). In a pre- and postnatal development study in rats, nateglinide administered by oral gavage at doses of 100, 300, and 1000 mg/kg/day from gestation day 17 to lactation day 21 resulted in lower body weight in offspring of rats administered nateglinide at 1,000 mg/kg/day (corresponding to 27 times the MHRD).

8.2 Lactation

Risk summary

There are no data on the presence of nateglinide in human milk, the effects on the breastfeeding infant, or the effects on milk production. The drug is present in animal milk. When a drug is present in animal milk, it is likely that the drug will be present in human milk (see Data). Because the potential for hypoglycemia in breast-fed infants, advise women that use of nateglinide is not recommended while breastfeeding.

Data

In rat reproduction studies, nateglinide and its metabolite are excreted in the milk following oral dose (300 mg/kg). The overall milk: plasma (M/P) concentration ratio of the total radioactivity was approximately 1.4 based on AUC0-48values. The M/P ratio of unchanged nateglinide was approximately 2.2.

8.4 Pediatric Use

The safety and effectiveness of nateglinide have not been established in pediatric patients.

8.5 Geriatric Use

436 patients 65 years and older, and 80 patients 75 years and older were exposed to nateglinide in clinical studies. No differences were observed in safety or efficacy of nateglinide between patients age 65 and over, and those under age 65. However, greater sensitivity of some older individuals to nateglinide therapy cannot be ruled out.

8.6 Renal Impairment

No dosage adjustment is recommended in patients with mild to severe renal impairment [see Clinical Pharmacology (12.3)].

8.7 Hepatic Impairment

No dose adjustment is recommended for patients with mild hepatic impairment. Use of nateglinide in patients with moderate-to-severe hepatic impairment has not been studied and therefore, should be used with caution in these patients [see Clinical Pharmacology (12.3)].

10 OVERDOSAGE

There have been no instances of overdose with nateglinide in clinical trials. However, an overdose may result in an exaggerated glucose-lowering effect with the development of hypoglycemic symptoms. Hypoglycemic symptoms without loss of consciousness or neurological findings should be treated with oral glucose and adjustments in dosage and/or meal patterns. Severe hypoglycemic reactions with coma, seizure, or other neurological symptoms should be treated with intravenous glucose. As nateglinide is highly protein bound, dialysis is not an efficient means of removing it from the blood.

11 DESCRIPTION

Nateglinide Tablets, USP are an oral blood glucose-lowering drug of the glinide class. Nateglinide, (-)-N-[(trans-4-isopropylcyclohexane)carbonyl]-D-phenylalanine, is structurally unrelated to the oral sulfonylurea insulin secretagogues.

The structural formula is as shown:

Nateglinide is a white powder with a molecular weight of 317.43. It is freely soluble in methanol, ethanol, and chloroform, soluble in ether, sparingly soluble in acetonitrile and octanol, and practically insoluble in water. Nateglinide biconvex tablets contain 60 mg, or 120 mg, of nateglinide for oral administration.

Inactive Ingredients:colloidal silicon dioxide, croscarmellose sodium, lactose monohydrate, magnesium stearate, microcrystalline cellulose, povidone, pregelatinized starch (starch 1500®). Starch 1500®is partially pregelatinized maize starch. The 60 mg also contains iron oxide red, polyethylene glycol, polyvinyl alcohol, talc, and titanium dioxide. In addition, the 120 mg contains FD&C Yellow #6/Sunset Yellow Aluminum Lake, iron oxide yellow.

12 CLINICAL PHARMACOLOGY

12.1 Mechanism of Action

Nateglinide lowers blood glucose levels by stimulating insulin secretion from the pancreas. This action is dependent upon functioning beta-cells in the pancreatic islets. Nateglinide interacts with the ATP-sensitive potassium (K^+ATP) channel on pancreatic beta-cells. The subsequent depolarization of the beta cell opens the calcium channel, producing calcium influx and insulin secretion. The extent of insulin release is glucose dependent and diminishes at low glucose levels. Nateglinide is highly tissue selective with low affinity for heart and skeletal muscle.

12.2 Pharmacodynamics

Nateglinide stimulates pancreatic insulin secretion within 20 minutes of oral administration. When nateglinide is dosed before meals, the peak rise in plasma insulin occurs approximately 1 hour after dosing and falls to baseline by 4 hours after dosing.

12.3 Pharmacokinetics

In patients with Type 2 diabetes, multiple dose administration of nateglinide over the dosage range of 60 mg to 240 mg shows linear pharmacokinetics for both area under the curve (AUC) and Cmax. In patients with Type 2 diabetes, there is no apparent accumulation of nateglinide upon multiple dosing of up to 240 mg three times daily for 7 days.

Absorption

Absolute bioavailability of nateglinide is approximately 73%. Plasma profiles are characterized by multiple plasma concentration peaks when nateglinide is administered under fasting conditions. This effect is diminished when nateglinide is taken prior to a meal. Following oral administration immediately prior to a meal, the mean peak plasma nateglinide concentrations (Cmax) generally occur within 1 hour (Tmax) after dosing. Tmaxis independent of dose.

The pharmacokinetics of nateglinide are not affected by the composition of a meal (high protein, fat, or carbohydrate). However, peak plasma levels are significantly reduced when nateglinide is administered 10 minutes prior to a liquid meal as compared to solid meal. When given with or after meals, the extent of nateglinide absorption (AUC) remains unaffected. However, there is a delay in the rate of absorption characterized by a decrease in Cmaxand a delay in time to peak plasma concentration (Tmax).

Nateglinide did not have any effect on gastric emptying in healthy subjects as assessed by acetaminophen testing.

Distribution

Following intravenous (IV) administration of nateglinide, the steady-state volume of distribution of nateglinide is estimated to be approximately 10 L in healthy subjects. Nateglinide is extensively bound (98%) to serum proteins, primarily serum albumin, and to a lesser extent α1acid glycoprotein. The extent of serum protein binding is independent of drug concentration over the test range of 0.1 to 10 mcg/mL.

Elimination

In healthy volunteers and patients with type 2 diabetes mellitus, nateglinide plasma concentrations declined with an average elimination half-life of approximately 1.5 hours.

Metabolism

In vitrodrug metabolism studies indicate that nateglinide is predominantly metabolized by the cytochrome P450 isozyme CYP2C9 (70%) and to a lesser extent CYP3A4 (30%).

The major routes of metabolism are hydroxylation followed by glucuronide conjugation. The major metabolites are less potent antidiabetic agents than nateglinide. The isoprene minor metabolite possesses potency similar to that of the parent compound nateglinide.

Excretion

Nateglinide and its metabolites are rapidly and completely eliminated following oral administration. Eighty-three percent of the 14C-nateglinide was excreted in the urine with an additional 10% eliminated in the feces. Approximately 16% of the 14C-nateglinide was excreted in the urine as parent compound.

Specific Populations

Renal Impairment

No pharmacokinetic data are available in subjects with mild renal impairment (CrCl 60 to 89 mL/min). Compared to healthy matched subjects, patients with type 2 diabetes mellitus and moderate and severe renal impairment (CrCl 15-50 mL/min) not on dialysis displayed similar apparent clearance, AUC, and Cmax.Patients with type 2 diabetes and renal failure on dialysis exhibited reduced overall drug exposure (Cmaxdecreased by 49%; not statistically significant). However, hemodialysis patients also experienced reductions in plasma protein binding compared to the matched healthy volunteers.

In a cohort of 8 patients with type 2 diabetes and end-stage renal disease (ESRD) (eGFR < 15 mL/min/1.73m^2) M1 metabolite accumulation up to 1.2 ng/mL occurred with a dosage of 90 mg once daily for 1 to 3 months. In another cohort of 8 patients with type 2 diabetes on hemodialysis, M1 concentration decreased after a single session of hemodialysis. Although the hypoglycemic activity of the M1 metabolite is approximately 5 times lower than nateglinide, metabolite accumulation may increase the hypoglycemic effect of the administered dose.

Hepatic Impairment

In patients with mild hepatic impairment, the mean increase in Cmaxand AUC of nateglinide were 37% and 30% respectively, as compared to healthy matched control subjects. There is no data on pharmacokinetics of nateglinide in patients with moderate-to-severe hepatic impairment.

Gender

No clinically significant differences in nateglinide pharmacokinetics were observed between men and women.

Race

Results of a population pharmacokinetic analysis including subjects of Caucasian, Black, and other ethnic origins suggest that race has little influence on the pharmacokinetics of nateglinide.

Age

Age does not influence the pharmacokinetic properties of nateglinide.

Drug Interactions:

In vitroassessment of drug interactions

Nateglinide is a potential inhibitor of the CYP2C9 isoenzyme in vivoas indicated by its ability to inhibit the in vitrometabolism of tolbutamide. Inhibition of CYP3A4 metabolic reactions was not detected in in vitroexperiments.

In vitrodisplacement studies with highly protein-bound drugs such as furosemide, propranolol, captopril, nicardipine, pravastatin, glyburide, warfarin, phenytoin, acetylsalicylic acid, tolbutamide, and metformin showed no influence on the extent of nateglinide protein binding. Similarly, nateglinide had no influence on the serum protein binding of propranolol, glyburide, nicardipine, warfarin, phenytoin, acetylsalicylic acid, and tolbutamide in vitro. However, prudent evaluation of individual cases is warranted in the clinical setting.

In vivoassessment of drug interactions

The effect of coadministered drugs on the pharmacokinetics of nateglinide and the effect of nateglinide on pharmacokinetics of coadministered drugs are shown in Tables 3 and 4. No clinically relevant change in pharmacokinetic parameters of either agent was reported when nateglinide was coadministered with glyburide, metformin, digoxin, warfarin, and diclofenac.

Table 3: Effect of Coadministered Drugs on Pharmacokinetics of Nateglinide
Coadministered drug | Dosing regimen of coadministered drug | Dosing regimen of nateglinide | Change in Cmax | Change in AUC
Glyburide | 10 mg once daily for 3 weeks | 120 mg three times a day, single dose | 8.78% ↓ | 3.53 % ↓
Metformin | 500 mg three times a day for 3 weeks | 120 mg three times a day, single dose | AM: 7.14% ↑ PM: 11.4% ↓ | AM: 1.51% ↑ PM: 5.97% ↑
Digoxin | 1 mg, single dose | 120 mg three times a day, single dose | AM: 2.17% ↓ PM: 3.19% ↑ | AM: 7.62% ↑ PM: 2.22% ↑
Warfarin | 30 mg, single dose | 120 mg three times a day for 4 days | 2.65% ↑ | 3.72% ↓
Diclofenac | 75 mg, single dose | 120 mg twice daily, single dose | AM: 13.23% ↓ *PM: 3.76% ↑ | AM: 2.2% ↓ *PM: 7.5% ↑
AM: after morning dose; PM: after evening dose; *after second dose; ↑: increase in the parameter; ↓: decrease in the parameter

Table 4: Effect of Nateglinide on Pharmacokinetics of Coadministered Drugs
Coadministered drug | Dosing regimen of coadministered drug | Dosing regimen of nateglinide | Change in Cmax | Change in AUC
Glyburide | 10 mg once daily for 3 weeks | 120 mg three times a day, single dose | 3.18% ↓ | 7.34% ↓
Metformin | 500 mg three times a day for 3 weeks | 120 mg three times a day, single dose | AM: 10.7% ↑ PM: 0.40% ↑ | AM: 13.3% ↑ PM: 2.27% ↓
Digoxin | 1 mg, single dose | 120 mg three times a day, single dose | 5.41% ↓ | 6.58 % ↑
Warfarin | 30 mg, single dose | 120 mg three times a day for 4 days | R-warfarin: 1.03% ↓ S-warfarin: 0.85% ↓ | R-warfarin: 0.74% ↑ S-warfarin: 7.23% ↑
Diclofenac | 75 mg, single dose | 120 mg twice daily, single dose | 2.19% ↑ | 7.97% ↑
AM: after morning dose; PM: after evening dose; SD: single dose; ↑: increase in the parameter; ↓: decrease in the parameter

13 NONCLINICAL TOXICOLOGY

13.1 Carcinogenesis, Mutagenesis, Impairment of Fertility

Carcinogenicity:Nateglinide did not increase tumors in two year carcinogenicity studies conducted in mice and rats. Oral doses of Nateglinide up to 900 mg/kg in rats and 400 mg/kg in mice were tested, which produced exposures in rats approximately 30-40 times and in mice 10-30 times the human therapeutic exposure of nateglinide at a dose of 120 mg three times daily, based on AUC.

Mutagenesis:Nateglinide was not genotoxic in the in vitroAmes test, mouse lymphoma assay, chromosome aberration assay or in the in vivomouse micronucleus test.

Impairment of Fertility:Fertility was unaffected by administration of nateglinide to rats at doses up to 600 mg/kg (corresponding to 16 times the MRHD of 120 mg three times per day, based on BSA).

14 CLINICAL STUDIES

14.1 Monotherapy

In a 24-week, double-blind, placebo-controlled study, patients with type 2 diabetes were randomized to receive either nateglinide (60 mg or 120 mg three times daily before meals) or placebo. Patients previously treated with antidiabetic medications were required to discontinue that medication for at least 2 months before randomization.

At Week 24, treatment with nateglinide before meals resulted in statistically significant reductions in mean HbA1C and mean fasting plasma glucose (FPG) compared to placebo (see Table 5). The reductions in HbA1C and FPG were similar for patient's naïve to, and those previously exposed to, antidiabetic medications.

Table 5: Endpoint Results for a 24-week, Fixed Dose Study of Nateglinide Monotherapy
 | Placebo | Nateglinide 60 mg three times daily before meals | Nateglinide 120 mg three times daily before meals
HbA1C(%) | N = 168 | N = 167 | N = 168
Baseline (mean) | 8.0 | 7.9 | 8.1
Change from baseline (mean) | +0.2 | -0.3 | -0.5
Difference from placebo (mean) |  | -0.5a | -0.7a
FPG (mg/dL) | N = 172 | N = 171 | N = 169
Baseline (mean) | 167.9 | 161.0 | 166.5
Change from baseline (mean) | +9.1 | +0.4 | -4.5
Difference from placebo (mean) |  | -8.7a | -13.6a
ap-value ≤ 0.004

14.2 Monotherapy Compared to Glyburide

In a 24-week, double-blind, active-controlled trial, patients with type 2 diabetes who had been on a sulfonylurea for 3 or more months and who had a baseline HbA1C greater than or equal to 6.5% were randomized to receive nateglinide (60 mg or 120 mg three times daily before meals) or glyburide 10 mg once daily. Patients randomized to nateglinide had statistically significant increases in mean HbA1C and mean FPG at endpoint compared to patients randomized to glyburide.

Table 6: Endpoint Results for a 24-Week Study of Nateglinide Monotherapy Compared to Glyburide
 | Glyburide 10 mg Once daily | Nateglinide 60 mg three times daily before meals | Nateglinide 120 mg three times daily before meals
HbA1c (%) | N = 183 | N = 178 | N = 179
Baseline (mean) | 7.8 | 8.0 | 7.9
Change from baseline (mean) | 0.3 | 1.3 | 1.1
Difference from glyburide |  | 1.0a | 0.9a
FPG (mmol/L) | N = 184 | N = 182 | N = 180
Baseline (mean) | 9.44 | 9.67 | 9.61
Change from baseline (mean) | 0.19 | 3.06 | 2.84
Difference from glyburide |  | 2.87a | 2.66a
ap-value < 0.001

14.3 Monotherapy and In Combination with Metformin

In a 24-week, double-blind, active- and placebo-controlled study, patients with type 2 diabetes were randomized to receive either nateglinide alone (120 mg three times daily before meals), metformin alone (500 mg three times daily), a combination of nateglinide 120 mg (three times daily before meals) and metformin (500 mg three times daily), or placebo. Fifty-seven percent of patients were previously untreated with oral antidiabetic therapy. Patients previously treated with antidiabetic medications were required to discontinue medication for at least 2 months before randomization.

At Week 24, statistically significant reductions in mean HbA1c and FPG were observed with metformin monotherapy compared to nateglinide monotherapy, and the combination of nateglinide and metformin compared to either nateglinide or metformin monotherapy (see Table 7).

Compared to placebo, nateglinide monotherapy was associated with a statistically significant increase in mean body weight, while no significant change in body weight was observed with metformin monotherapy or combination of nateglinide and metformin therapy (see Table 7). Among the subset of patients previously treated with other antidiabetic agents, primarily glyburide, HbA1C in the nateglinide monotherapy group increased slightly from baseline, whereas HbA1C was reduced in the metformin monotherapy group (see Table 7).

Table 7: Endpoint Results for a 24-Week Study of Nateglinide Monotherapy and Combination with Metformin
 | Placebo | Nateglinide 120 mg three times daily before meals | Metformin 500 mg three times daily | Nateglinide 120 mg before meals plus Metformin*
HbA1C (%)
All | N = 160 | N = 171 | N = 172 | N = 162
Baseline (mean) | 8.3 | 8.3 | 8.4 | 8.4
Change from baseline (mean) | +0.4 | -0.4bc | -0.8c | -1.5
Difference from placebo |  | -0.8a | -1.2a | -1.9a
Naїve | N = 98 | N = 99 | N = 98 | N = 81
Baseline (mean) | 8.2 | 8.1 | 8.3 | 8.2
Change from baseline (mean) | +0.3 | -0.7c | -0.8c | -1.6
Difference from placebo |  | -1.0a | -1.1a | -1.9a
Non-Naїve | N = 62 | N = 72 | N = 74 | N = 81
Baseline (mean) | 8.3 | 8.5 | 8.7 | 8.7
Change from baseline (mean) | +0.6 | +0.004bc | -0.8c | -1.4
Difference from placebo |  | -0.6a | -1.4a | -2.0a
FPG (mg/dL)
All | N = 166 | N = 173 | N = 174 | N = 167
Baseline (mean) | 194.0 | 196.5 | 196.0 | 197.7
Change from baseline (mean) | +8.0 | -13.1bc | -30.0c | -44.9
Difference from placebo |  | -21.1a | -38.0a | -52.9a
ap-value ≤ 0.05 vs. placebo
bp-value ≤ 0.03 vs. metformin
cp-value ≤ 0.05 vs. combination
*Metformin was administered three times daily

In another 24-week, double-blind, placebo-controlled trial, patients with type 2 diabetes with HbA1C greater than or equal to 6.8% after treatment with metformin (greater than or equal to 1500 mg daily for at least 1 month) were first entered into a four week run-in period of metformin monotherapy (2000 mg daily) and then randomized to receive either nateglinide (60 mg or 120 mg three times daily before meals) or placebo as add-on to metformin. At the end of treatment, nateglinide 60 mg and 120 mg three times daily resulted in a statistically significantly greater reductions in HbA1C compared to placebo when added to metformin (-0.4% and -0.6% for nateglinide 60 mg and nateglinide 120 mg plus metformin, respectively).

Table 8: Endpoint Results for a 24-Week Study of Nateglinide Monotherapy as Add-on to Metformin
 | Placebo + metformin | Nateglinide 60 mg + metformin | Nateglinide 120 mg + metformin
HbA1c(%) | N = 150 | N = 152 | N = 154
Baseline (mean) | 8.2 | 8.0 | 8.2
Change from baseline (mean) | 0.01 | -0.4 | -0.6
Difference from metformin |  | -0.4a | -0.6b
ap-value 0.003 vs. metformin
bp-value < 0.001 vs. metformin
All nateglinide/placebo taken three times daily before meals; all metformin 1000 mg twice daily

14.4 Add-On Combination Therapy with Rosiglitazone

A 24-week, double blind, multicenter, placebo-controlled trial was performed in patients with type 2 diabetes not adequately controlled on rosiglitazone 8 mg daily. The addition of nateglinide (120 mg three times per day with meals) was associated with statistically significantly greater reductions in HbA1C compared to placebo as add-on to rosiglitazone. The mean change in weight from baseline was +3 kg for patients treated with nateglinide compared to +1 kg for patients treated with placebo when added to rosiglitazone.

Table 9: Endpoint Results for a 24-Week Study of the Effect of Adding Nateglinide or Placebo to Rosiglitazone
 | Placebo + rosiglitazone 8 mg once daily | Nateglinide 120 mg before meals + rosiglitazone 8 mg once daily
HbA1c (%) | N = 191 | N = 194
Baseline (mean) | 8.4 | 8.3
Change from baseline (mean) | 0.03 | -0.7
Difference from rosiglitazone (mean) |  | -0.7a
ap-value ≤ 0.0001

14.5 Add-On Combination Therapy with Glyburide

In a 12-week study of patients with type 2 diabetes inadequately controlled on glyburide 10 mg once daily, the addition of nateglinide (60 mg or 120 mg three times daily before meals) did not produce any additional benefit.

Table 10: Endpoint Results for a 12-week Study of the Effect of Adding Nateglinide or Placebo to Glyburide
 | Placebo + glyburide 10 mg once daily | Nateglinide 60 mg before meals + glyburide 10 mg once daily | Nateglinide 120 mg before meals + glyburide 10 mg once daily
HbA1c (%) | N = 58 | N = 55 | N = 54
Baseline (mean) | 8.7 | 8.7 | 8.7
Change from baseline (mean) | 0.3 | 0.2 | -0.02
Difference from glyburide (mean) |  | -0.1a | -0.3b
Placebo or nateglinide given 10 minutes prior to breakfast, lunch, and dinner; glyburide given with the breakfast dose of nateglinide or placebo.
ap-value 0.6959
bp-value 0.1246

16 HOW SUPPLIED/STORAGE AND HANDLING

How Supplied

Nateglinide Tablets, USP are supplied in the following package and dose strength forms:

60 mg

Pink color coated, round biconvex, beveled edge tablet debossed with "P 984" on one side and plain on the other side.

Bottles of 100……………NDC 51407-656-01

120 mg

Orange color coated, oval shaped biconvex, tablet debossed with "P 985" on one side and plain on the other side.

Bottles of 100……………NDC 51407-657-01

Storage and Handling

Store at 25°C (77°F); excursions permitted to 15°C-30°C (59°F-86°F). [See USP Controlled Room Temperature]

Dispense in a tight, light resistant container.

17 PATIENT COUNSELING INFORMATION

Administration

Instruct patients to take nateglinide 1 to 30 minutes before meals. Instruct patients that skip meals to skip their dose of nateglinide [see Dosage and Administration (2)].

Hypoglycemia

Inform patients that nateglinide can cause hypoglycemia and instruct patients and their caregivers on self-management procedures, including glucose monitoring and management of hypoglycemia. Inform patients that their ability to concentrate and react may be impaired as a result of hypoglycemia. In patients at higher risk for hypoglycemia and patients who have reduced symptomatic awareness of hypoglycemia, increased frequency of blood glucose monitoring is recommended [see Warnings and Precautions (5.1)].

Lactation

Advise patients that use of nateglinide is not recommended while breastfeeding [see Use in Specific Populations (8.2)].

Drug Interactions

Discuss potential drug interactions with patients and inform them of potential drug-drug interactions with nateglinide.

Distributed by:

Strides Pharma Inc.

East Brunswick, NJ 00816

Rev. 02/2022

OS984-01-1-11

Marketed by:

GSMS, Inc.

Camarillo, CA 93012 USA

PACKAGE LABEL PRINCIPAL DISPLAY PANEL

Package Label

Rx Only

NDC 51407-656-01

Nateglinide Tablets

60 mg

100 Tablets.

PACKAGE LABEL PRINCIPAL DISPLAY PANEL

Package Label

Rx Only

NDC 51407-657-01

Nateglinide Tablets

120 mg

100 Tablets